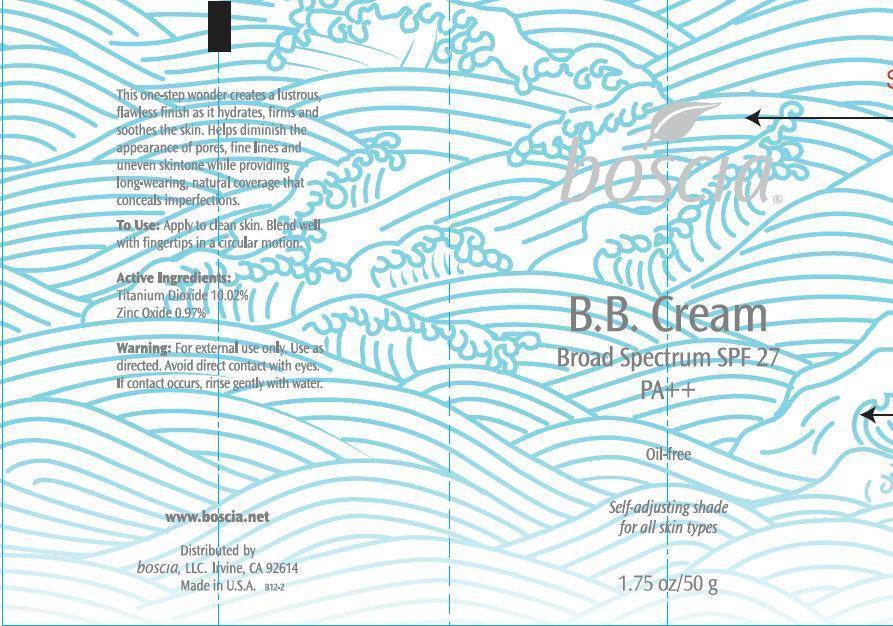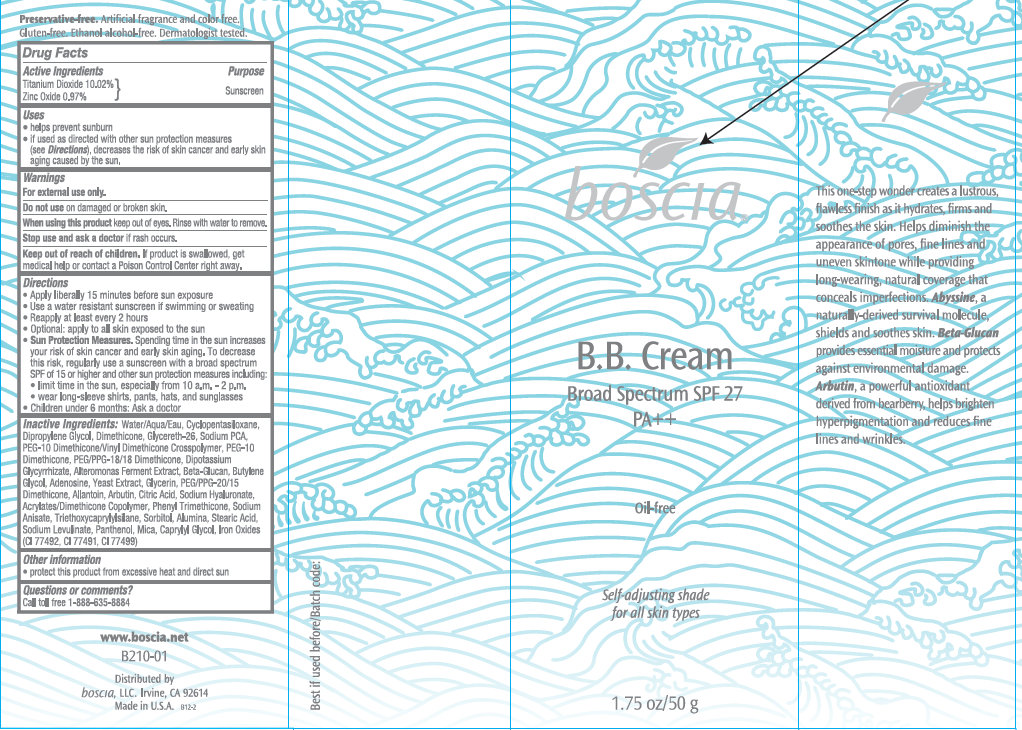 DRUG LABEL: Boscia BB Broad Spectrum SPF 27 PA Self Adjusting Shade
NDC: 76151-211 | Form: CREAM
Manufacturer: Boscia LLC
Category: otc | Type: HUMAN OTC DRUG LABEL
Date: 20231212

ACTIVE INGREDIENTS: TITANIUM DIOXIDE 10.02 g/100 g; ZINC OXIDE 0.97 g/100 g
INACTIVE INGREDIENTS: WATER; CYCLOMETHICONE 5; DIPROPYLENE GLYCOL; DIMETHICONE; GLYCERETH-26; SODIUM PYRROLIDONE CARBOXYLATE; PEG/PPG-18/18 DIMETHICONE; GLYCYRRHIZINATE DIPOTASSIUM; GLYCERIN; PEG/PPG-20/15 DIMETHICONE; ALLANTOIN; CITRIC ACID MONOHYDRATE; HYALURONATE SODIUM; PHENYL TRIMETHICONE; SODIUM ANISATE; TRIETHOXYCAPRYLYLSILANE; SORBITOL; ALUMINUM OXIDE; STEARIC ACID; SODIUM LEVULINATE; PANTHENOL; MICA; CAPRYLYL GLYCOL; FERRIC OXIDE YELLOW; FERRIC OXIDE RED; FERROSOFERRIC OXIDE

Boscia BB Cream Broad Spectrum SPF 27 PA Oil-Free Self Adjusting Shade

Active Ingredients

Titanium Dioxide 10.02% Zinc Oxide 0.97%

Purpose

Sunscreen

Uses

- helps prevent sunburn

- if used as directed with other sun protection measures (see), decreases the risk of skin cancer and early skin aging caused by the sun. Directions

Warnings

For external use only.

Do not use

on damaged or broken skin.

When using this product

keep out of eyes. Rinse with water to remove.

Stop use and ask a doctor

if rash occurs.

Keep out of reach of children.

If product is swallowed, get medical help or contact a Poison Control Center right away.

Directions

- Apply liberally 15 minutes before sun exposure
- Use a water resistant sunscreen if swimming or sweating
- Reapply at least every 2 hours
- Optional: apply to all skin exposed to the sun
- . Spending time in the sun increases your risk of skin cancer and early skin aging. To decrease this risk regularly use a sunscreen with a broadspectrum SPF of 15 or higher and another sun protection measures including: Sun Protection Measures
- Limit time in the usn, especially from 10 a.m. - 2 p.m.
- wear long-sleeve shirts, pants, hats, and sunglasses.
- Children under 6 months: Ask a doctor

Inactive Ingredients:

Water/Aqua/Eau, Cyclopentasiloxane, Dipropylene Glycol, Dimethicone, Glycereth-26, Sodium PCA, PEG-10 Dimethicone/Vinyl Dimethicone Crosspolymer, PEG-10 Dimethicone , PEG/PPG-18/18 Dimethicone, Dipotassium Glycyrrhizinate, Alteromonas Ferment Extract, Beta-Glucan, Butylene Glycol, Adenosine, Yeast Extract, Glycerin, PEG/PPG-20/15 Dimethicone, Allantoin, Arbutin, Citric Acid, Sodium Hyaluronate, Acrylates/Dimethicone Copolymer, Phenyl Trimethicone, Sodium Anisate,Triethoxycaprylylsilane, Sorbitol, Alumina, Stearic Acid, Sodium Levulinate, Panthenol, Mica, Caprylyl Glycol, Iron Oxides, (CI 77492, CI 77491, CI 77499)

Other Information

- Protect this product from excessive heat and direct sun

boscia B.B. Cream Broad Spectrum

This one-step wonder creates a lustrous, flawless finish as it hydrates, firms and soothes the skin. Helps diminish the appearances of pores, fine lines and uneven skintone while providing long-wearing, natural coverage that conceals imperfections. , a naturally-derived survival mollecule, shields and soothes skin, provides essential moisture and protects against environmental damage. a powerful antioxidant derived from bearberry, helps brighten hyperpigmentation and reduces fine lines and wrinkles Abyssine Beta-Glucan Arbutin,

. Artificial fragrance and color free. Gluten-free. Ethanol alcohol-free. Dermatologist tested. Preservative-Free

PACKAGE LABEL

boscia B.B. Cream Broad Spectrum SPF 27 PA++ Oil-Free Self-adjusting shade for all skin types 1.75oz/50 g